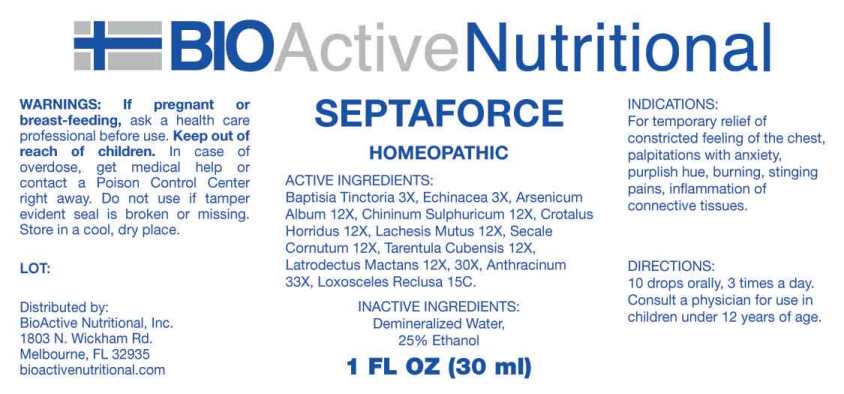 DRUG LABEL: Septaforce
NDC: 43857-0620 | Form: LIQUID
Manufacturer: BioActive Nutritional, Inc.
Category: homeopathic | Type: HUMAN PRESCRIPTION DRUG LABEL
Date: 20241018

ACTIVE INGREDIENTS: BAPTISIA TINCTORIA ROOT 3 [hp_X]/1 mL; ECHINACEA ANGUSTIFOLIA WHOLE 3 [hp_X]/1 mL; ARSENIC TRIOXIDE 12 [hp_X]/1 mL; QUININE SULFATE 12 [hp_X]/1 mL; CROTALUS HORRIDUS HORRIDUS VENOM 12 [hp_X]/1 mL; LACHESIS MUTA VENOM 12 [hp_X]/1 mL; CLAVICEPS PURPUREA SCLEROTIUM 12 [hp_X]/1 mL; CITHARACANTHUS SPINICRUS 12 [hp_X]/1 mL; LATRODECTUS MACTANS 12 [hp_X]/1 mL; BACILLUS ANTHRACIS IMMUNOSERUM RABBIT 33 [hp_X]/1 mL; LOXOSCELES RECLUSA 15 [hp_C]/1 mL
INACTIVE INGREDIENTS: WATER; ALCOHOL

DRUG FACTS:

ACTIVE INGREDIENTS:

Baptisia Tinctoria 3X, Echinacea (Angustifolia) 3X, Arsenicum Album 12X, Chininum Sulphuricum 12X, Crotalus Horridus 12X, Lachesis Mutus 12X, Secale Cornutum 12X, Tarentula Cubensis 12X, Latrodectus Mactans 12X, 30X, Anthracinum 33X, Loxosceles Reclusa 15C.

INDICATIONS:

For temporary relief of constricted feeling of the chest, palpitations with anxiety, purplish hue, burning, stinging pains, inflammation of connective tissues.

WARNINGS:

If pregnant or breast-feeding, ask a health care professional before use.

Keep out of reach of children. In case of overdose, get medical help or contact a Poison Control Center right away.

Do not use if tamper evident seal is broken or missing.

Store in cool, dry place.

Keep out of reach of children. In case of overdose, get medical help or contact a Poison Control Center right away.

DIRECTIONS:

10 drops orally, 3 times a day. Consult a physician for use in children under 12 years of age.

INDICATIONS:

For temporary relief of constricted feeling of the chest, palpitations with anxiety, purplish hue, burning, stinging pains, inflammation of connective tissues.

INACTIVE INGREDIENTS:

Demineralized Water, 25% Ethanol

QUESTIONS:

Distributed by:
BioActive Nutritional, Inc.
1803 N. Wickham Rd.
Melbourne, FL 32935
bioactivenutritional.com

PACKAGE LABEL DISPLAY:

BIOActive Nutritional

SEPTAFORCE

HOMEOPATHIC

1 FL OZ (30 ml)